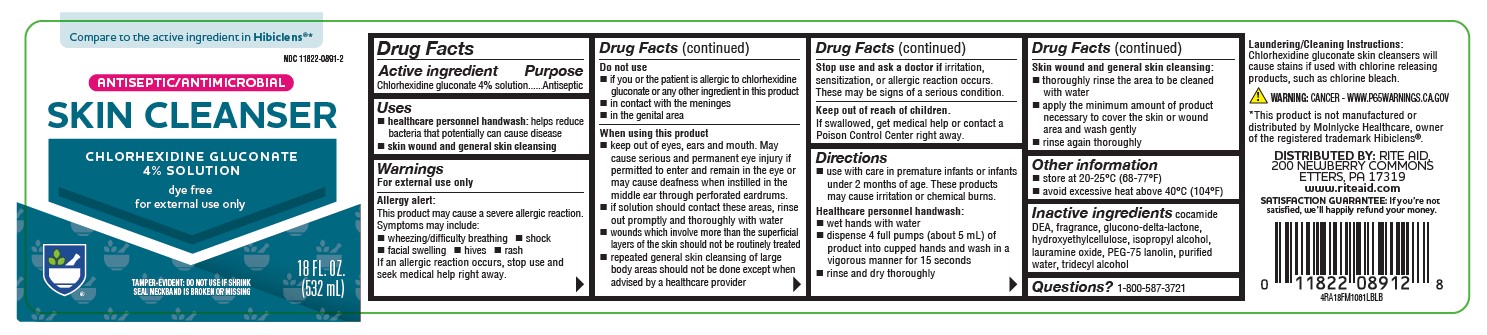 DRUG LABEL: Antiseptic Skin Cleanser
NDC: 11822-0891 | Form: SOLUTION
Manufacturer: Rite Aid
Category: otc | Type: HUMAN OTC DRUG LABEL
Date: 20231109

ACTIVE INGREDIENTS: CHLORHEXIDINE GLUCONATE 4 g/100 mL
INACTIVE INGREDIENTS: DIHYDROXYETHYL LAURAMINE OXIDE; PEG-75 LANOLIN; HYDROXYETHYL CELLULOSE (2000 CPS AT 1%); WATER; TRIDECYL ALCOHOL; GLUCONOLACTONE; ISOPROPYL ALCOHOL; COCO DIETHANOLAMIDE

4% Rite Aid 18oz FM

Active ingredient

Chlorhexidine gluconate 4% solution

Purpose

Antiseptic

Uses

healthcare personnel handwash: helps reduce bacteria that potentially can cause disease

skin wound and general skin cleansing

Warnings

For external use only

Allergy alert:

This product may cause a severe allergic reaction. Symptoms may include:

- wheezing/difficulty breathing
- shock
- facial swelling
- hives
- rash

If an allergic reaction occurs, stop use and seek medical help right away.

Do not use

- if you or the patient is allergic to chlorhexidine gluconate or any other ingredient in this product
- in contact with the meninges
- in the genital area

When using this product

- keep out of eyes, ears and mouth. May cause serious and permanent eye injury if permitted to enter and remain in the ete or may cause deafness when instilled in the middle ear through perforated eardurms.
- if solution should contact these areas, rinse out promptly and thoroughly with water
- wounds which involve more than the superficial layers of the skin should not be routinely treated
- repeated general skin cleansing of large body areas should not be done except when advised by a healthcare provider

Stop use and ask a doctor if

irritation, sensitization, or allergic reaction occurs. These may be signs of a serious condition.

Keep out of reach of children.

If swallowed, get medical help or contact a Poison Control Center right away.

Directions

- use with care in premature infants or infants under two months of age. These products may cause irritation or chemical burns.

Healthcare personnel handwash:

- wet hands with water
- dispense 4 full pumps (6 grams) of product into cupped hands and wash in a vigrous manner for 15 seconds
- rinse and dry thoroughly

Skin wound and general skin cleansing:

- thoroughly rinse the area to be cleaned with water
- apply the minimum amount of product necessary to cover the skin or wound area and wash gently
- rinse again thoroughly

Other information

- store at 20-25°C (68-77°F)
- avoid excessive heat above 40°C (104°F)

Inactive ingredients

cocamide DEA, fragrance, glucono-delta-lactone, hydroxyethylcellulose, isopropyl alcohol, lauramine oxide, PEG-75 lanolin, purified water, tridecyl alcohol

Questions or comments?

1-800-587-3721

RECENT MAJOR CHANGES

Uses: removal of surgical handscrub indication (11/23)

Directions: removal of surgical handscurb indication (11/23)

OTHER SAFETY INFORMATION

Laundering/Cleaning Instructions: Chlorhexidine gluconate skin cleansers will cause stains if used with chlorine releasing products, such as chlorine bleach.

WARNING: CANCER - WWW.P65WARNINGS.CA.GOV

PACKAGE LABEL

Compare to the active ingredient in Hibiclens®*

NDC 11822-0891-2

ANTISEPTIC/ANTIMICROBIAL

SKIN CLEANSER

CHLORHEXIDINE GLUCONATE

4% SOLUTION

dye free

for external use only

TAMPER-EVIDENT: DO NOT USE IF SHRINK SEAL NECKBAND IS BROKEN OR MISSING

18 FL OZ (532 mL)

4RA18FM1061LBLB

*This product is not manufactured or distributed by Molnlycke Healthcare, owner of the registered trademark Hibiclens®.

DISTRIBUTED BY: RITE AID, 200 NEWBERRY COMMONS
ETTERS, PA 17319
www.riteaid.com
SATISFACTION GUARANTEE: If you’re not satisfied, we’ll happily refund your money.